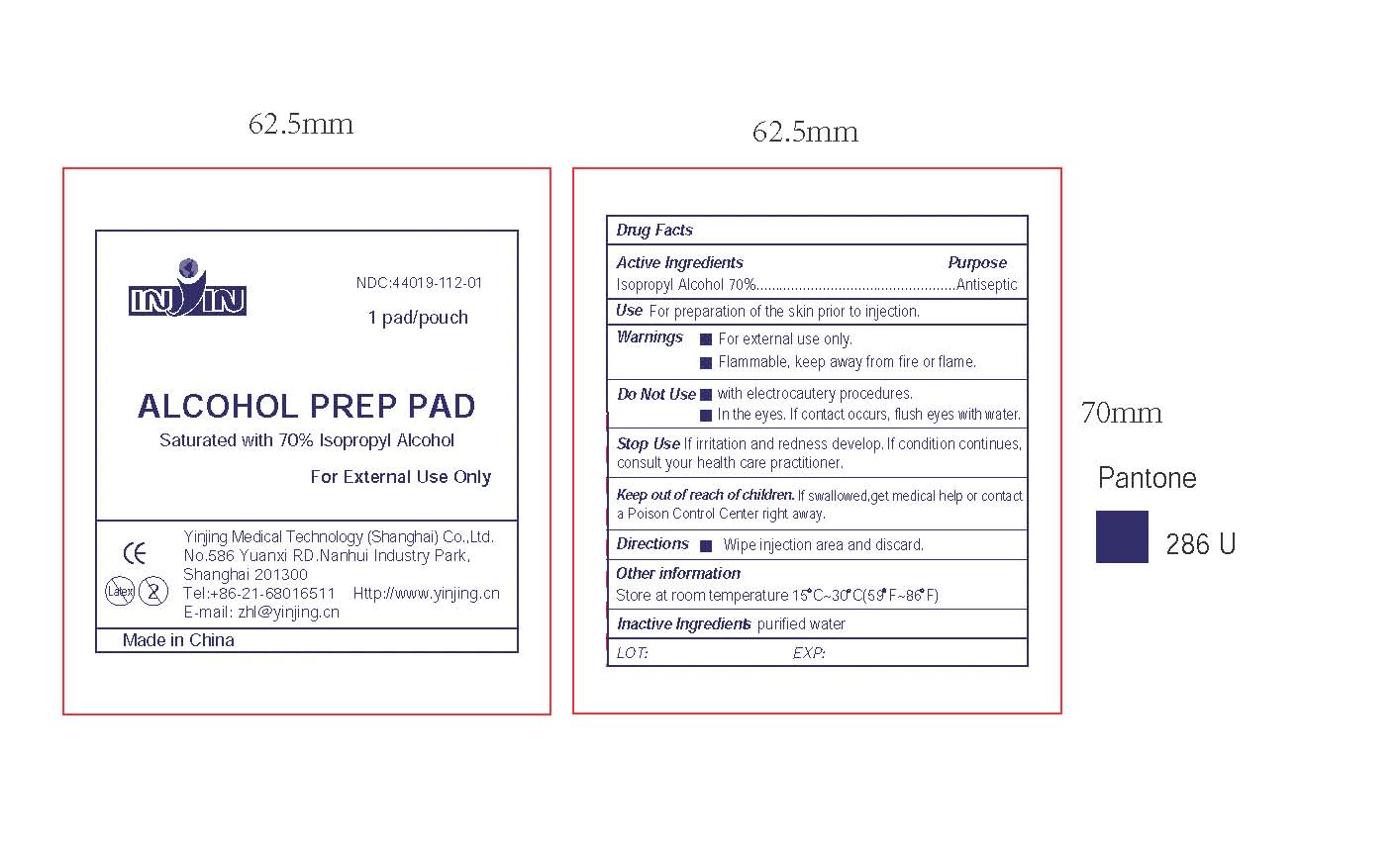 DRUG LABEL: ALCOHOL PREP PAD - LARGE

NDC: 44019-112 | Form: SWAB
Manufacturer: Yinjing Medical Technology (Shanghai) Co., Ltd.
Category: otc | Type: HUMAN OTC DRUG LABEL
Date: 20160824

ACTIVE INGREDIENTS: ISOPROPYL ALCOHOL 70 g/100 g
INACTIVE INGREDIENTS: WATER

ALCOHOL PREP PAD - LARGE

Active Ingredients

Isopropyl Alcohol 70%

Purpose

Antiseptic

Use

For preparation of the skin prior to injection.

Warnings

- For external use only.
- Flammable, keep away from fire or flame.

Do Not Use

- with electrocautery procedures.
- In the eyes. If contact occurs, flush eyes with water.

Stop Use

If irritation and redness develop. If condition continues, consult your health care practitione.

Keep out of reach of children.

If swallowed,get medical help or contact a Poison Control Center right away.

Directions

- Wipe injection area and discard.

Other information

Store at room temperature 15 C~30 C(59 F~86 F)

Inactive Ingredients

purified water

Shanghai Yinjing Medical Supplies Co., Ltd.
No.586 Yuanxi RD.Nanhui Industry Park,
Shanghai 201300
Tel:+86-21-68016633 Http://www.yinjing.cn
E-mail: zhl@yinjing.cn
Made in China
LOT: EXP:

PACKAGE LABEL

inin
NDC:44019-112-01

1 pad/pouch
ALCOHOL PREP PAD
Saturated with 70% Isopropyl Alcohol
For External Use Only